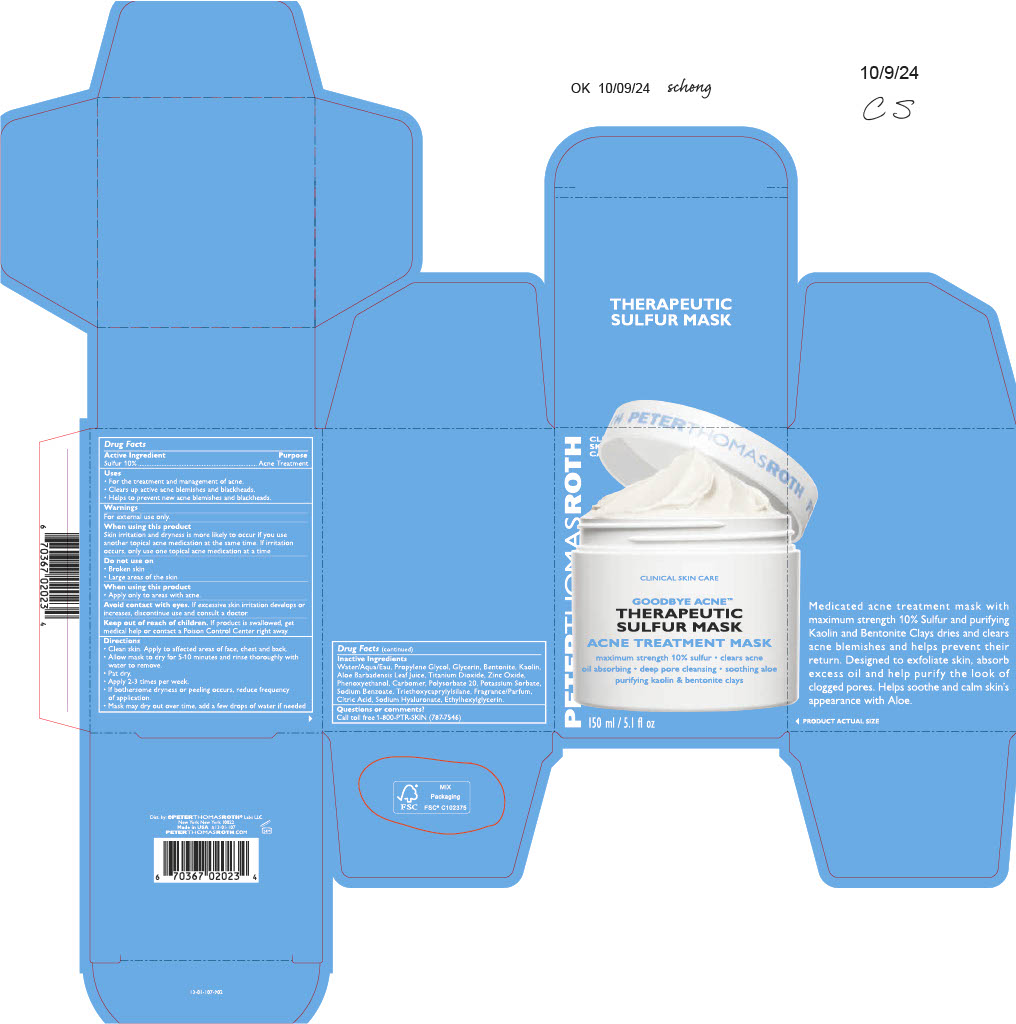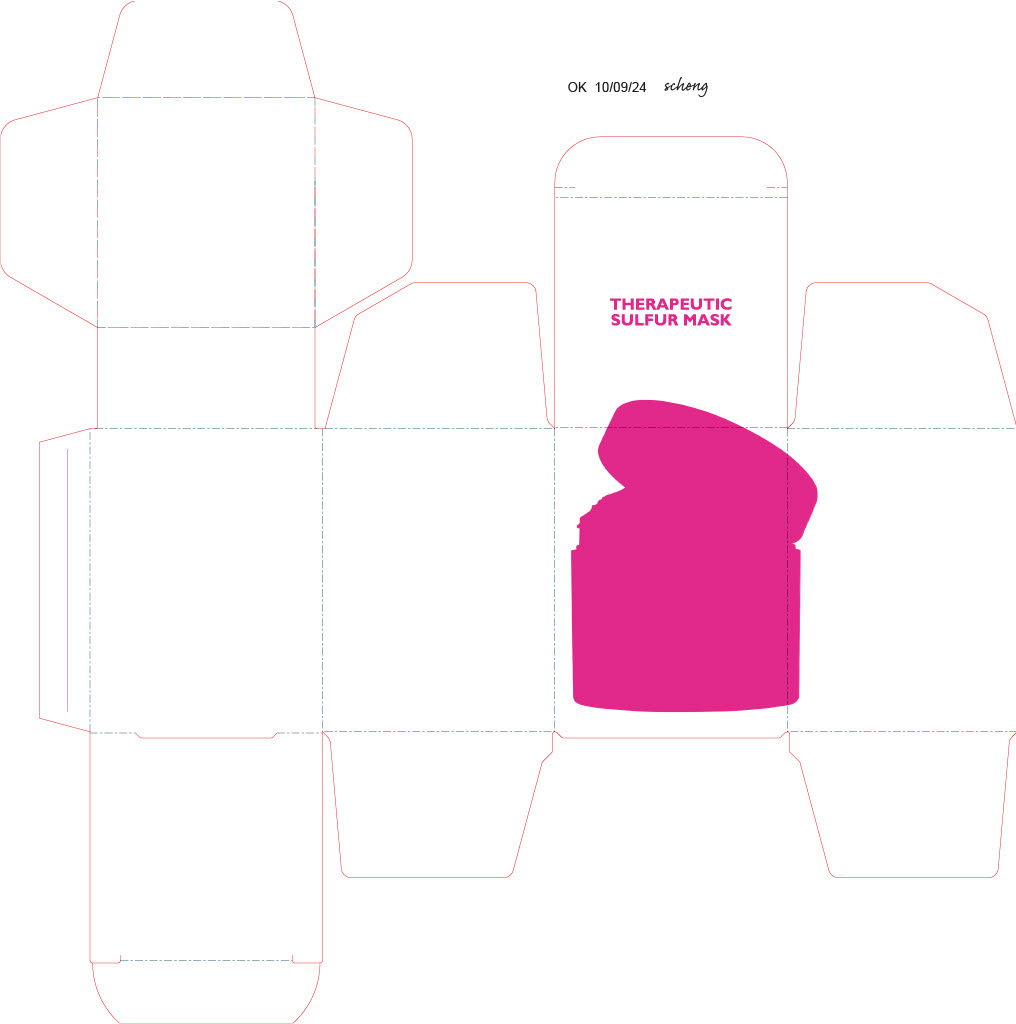 DRUG LABEL: GOODBYE ACNE THERAPEUTIC SULFUR MASK
NDC: 54031-107 | Form: PASTE
Manufacturer: PETER THOMAS ROTH, LLC
Category: otc | Type: HUMAN OTC DRUG LABEL
Date: 20250317

ACTIVE INGREDIENTS: SULFUR 14.458 g/144.58 g
INACTIVE INGREDIENTS: CARBOMER; PHENOXYETHANOL; BENZYL ACETATE; WATER; POLYSORBATE 20; SODIUM BENZOATE; HEXAMETHYLINDANOPYRAN; AMYL SALICYLATE; ETHYLHEXYLGLYCERIN; ANISALDEHYDE; HELIOTROPINE; BENTONITE; POTASSIUM SORBATE; SODIUM HYALURONATE; LINALOOL; ALOE BARBADENSIS LEAF JUICE; PROPYLENE GLYCOL; CITRONELLOL; KAOLIN; BENZYL SALICYLATE; LINALYL ACETATE; PHENYLETHYL ALCOHOL; TRIETHOXYCAPRYLYLSILANE; TITANIUM DIOXIDE; TERPINEOL ACETATE; LIMONENE, (+)-; GLYCERIN; CITRIC ACID; ZINC OXIDE

PTR 13-01-107 SULFUR MASK 5oz, 1.7oz and 0.5oz (JJL# ref = Formula 31-16-1 v6)

ACTIVE INGREDIENT

SULFUR 10%................................................................Acne Treatment

USES

- For the treatment and management of acne.
- Clears up active acne blemishes and blackheads.
- Helps to prevent new acne blemishes and blackheads.

WARNINGS

For external use only.

When Using this product

Skin irritation and dryness is more likely to occur if you use another topical acne medication at the same time. If irritation occurs, only use one topical acne medication at a time.

- Apply only to areas with Acne

Avoid contact with eyes. If excessive skin irritation develops or increases, discontinue use abd consult a doctor.

Do not use on

- Broken skin
- Large areas of the skin

KEEP OUT OF REACH OF CHILDREN

If product is swallowed, get medical help or contact a Poison Control Center right away.

Directions

- Clean skin. Apply to affected areas of face, chest and back.
- Allow mask to dry for 5-10 minutes and rinse thoroughly with water to remove.
- Pat dry.
- Apply 2-3 times per week.
- If bothersome dryness or peeling occurs, reduce frequency of application
- Mask may dry out over time, add a few drops of water if needed.

Inactive Ingredients

Water/Aqua/eau, Propylene Glycol, Glycerin, Bentonite, Kaolin, Aloe Barbadensis Leaf Juice, Titanium Dioxide, Zinc Oxide, Phenoxyethanol, Carbomer, Polysorbate 20, Potassium Sorbate, Sodium benzoate, triethoxycaprylylsilane, Fragrane/Parfum, Citric Acid, Sodium Hyaluronate, Ethylhexylglycerin.

Questions or Comments?

Call toll free 1-800-PTR-SKIN (787-7546)

PURPOSE

Sulfur 10%..................................................................................Acne treatment